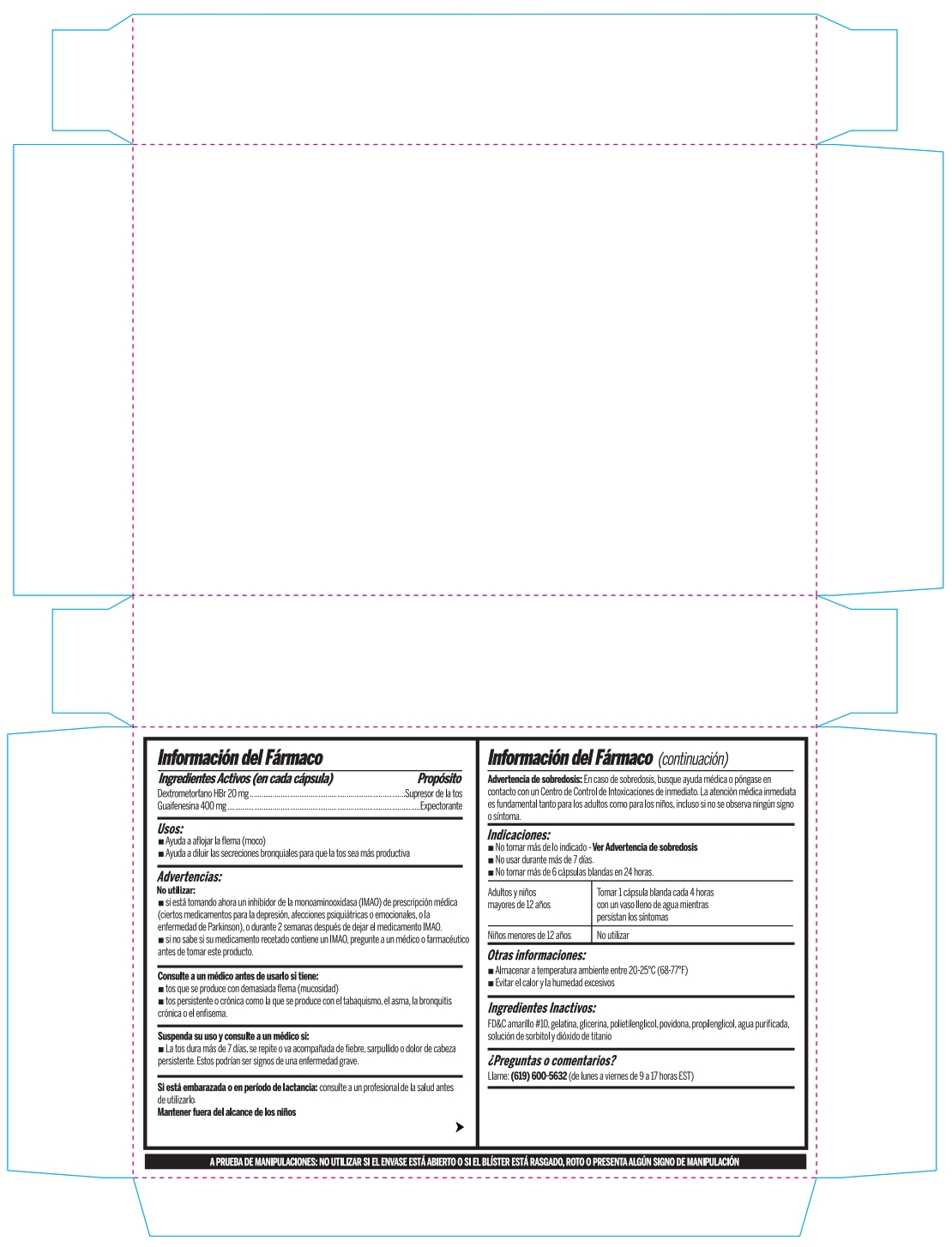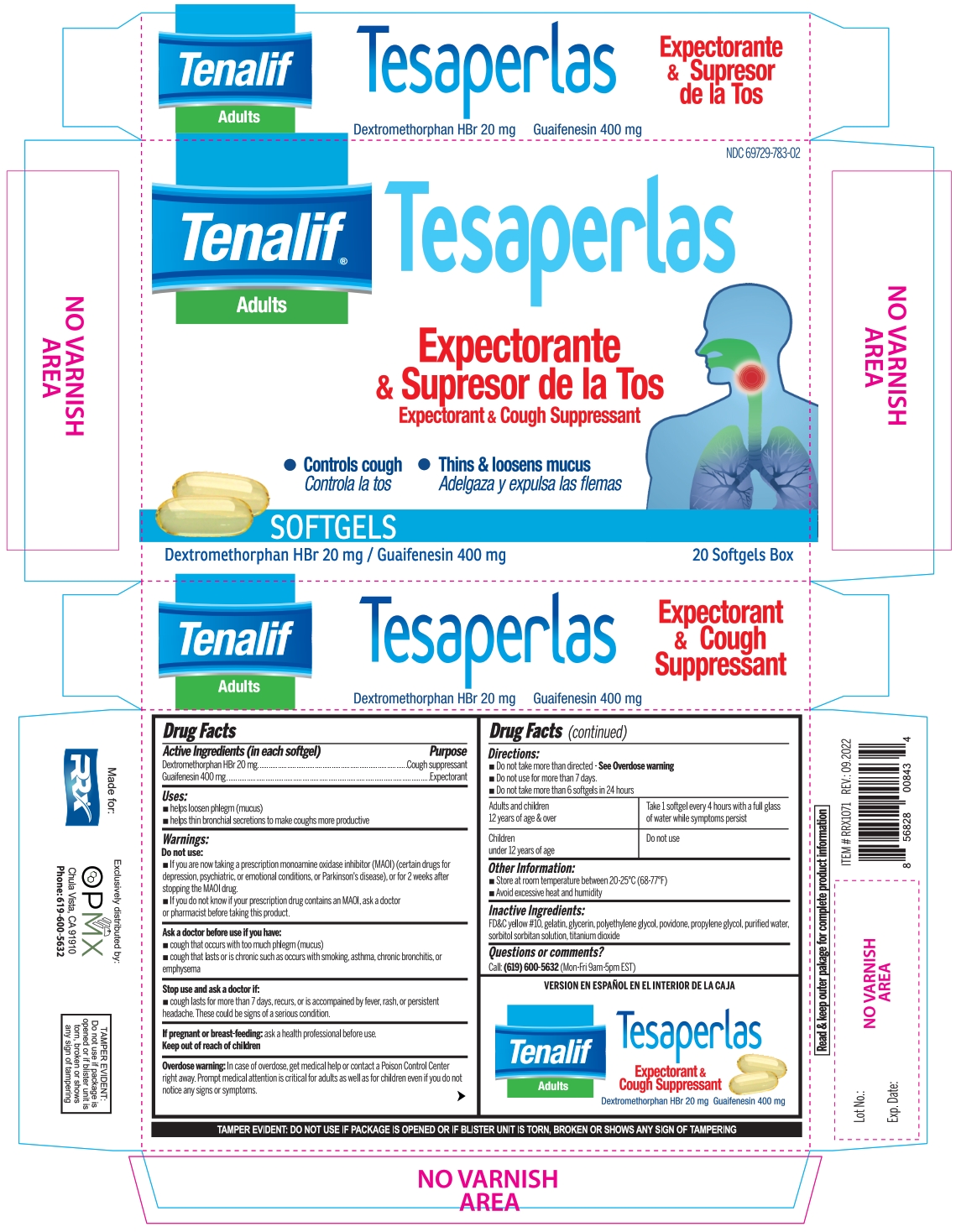 DRUG LABEL: GUAIFENESIN, DEXTROMETHORPHAN HBR
NDC: 69729-783 | Form: CAPSULE, LIQUID FILLED
Manufacturer: OPMX LLC
Category: otc | Type: HUMAN OTC DRUG LABEL
Date: 20240517

ACTIVE INGREDIENTS: GUAIFENESIN 400 mg/1 1; DEXTROMETHORPHAN HYDROBROMIDE 20 mg/1 1
INACTIVE INGREDIENTS: WATER; PROPYLENE GLYCOL; SORBITOL SOLUTION; POLYETHYLENE GLYCOL, UNSPECIFIED; GLYCERIN; GELATIN; POVIDONE, UNSPECIFIED; D&C YELLOW NO. 10; SORBITAN; TITANIUM DIOXIDE

TENALIF
(DEXTROMETHORPHAN HBR 20MG, GUAIFENESIN 400MG SOFTGEL)

Drug facts

ACTIVE INGREDIENT

Active ingredients (in each softgel) | Purpose
Dextromethorphan HBr 20 mg | Cough Suppressant
Guaifenesin 400 mg | Expectorant

Uses

helps looseen phlegm (mucus)
helps thin bronchial secretions to make coughs more productive

WARNINGS

Do not use

if you are now taking a prescription monoamine oxidase inhibitor (MAOI) (certain drugs for depression, psychiatric, or emotional conditions, or Parkinson's disease), or for 2 weeks after stopping the MAOI drug.
If you do not know if your prescription drug contains an MAOI, ask a doctor or pharmacist before taking this product.

Ask a doctor before use if you have

cough that occurs with too much phlegm (mucus)
cough that lasts or is chronic such as occurs with smooking, asthma, chronic bronchitis, or emphysema

Stop use and ask a doctor if

cough lasts for more than 7 days, recurs, or is accompained by fever, rash, or persistent headache. These could be signs of a serious condition.

If pregnant or breast-feeding

ask a health professional before use

Keep out of reach of children.

Overdose warning

In case of overdose, get medical help or contact a Poison Control Center right away. Prompt medical attention is critical for adults as well as for children even if you do not notice any signs or symptoms

Directions

Do not take more than directed - See Overdose warning
Do not use for more than 7 days.
Do not take more than 6 softgels in 24 hours

Adults and children 12 years of age & over:

Take 1 softgel every 4 hours with a full glass of water while symptoms persist

Children under 12 years of age:

Do not use

Other information

Store at room temperature between 20-25°C (68-77°F)
Avoid excessive heat and humiditydity

INACTIVE INGREDIENT

D&C yellow No. 10, gelatin, glycerin, polyethylene glycol, povidone, propylene glycol, purified water, sorbitol sorbitan solution, titanium dioxide.

Questions or comments?

Call: (619) 600-5632 (Mon-Fri 9am-5pm EST)

VERSIÓN EN ESPAÑOL EN EL INTERIOR DE LA CAJA

Tenalif - Adults
Tesaperlas
Expectorant & Cough Suppressant
Dextromethorphan HBr 20 mg Guaifenesin 400 mg

TAMPER EVIDENT: DO NOT USE IF PACKAGE IS OPENED OR IF BLISTER UNIT IS TORN, BROKEN OR SHOWS ANY SIGN OF TAMPERING

Tenalif
Adults
Tesaperlas
Dextromethorphan HBr 20 mg
Guaifenesin 400 mg
Expectorant & Cough Suppressant

Made for:
RRX

Exclusively distributed by:
OPMX
Chula Vista, CA 91910
Phones: 619-600-5632

TAMPER EVIDENT:
Do not use if package is opened or if blister unit is torn, broken or shows any sign of tampering

PRINCIPAL DISPLAY PANEL

NDC 69729-783-02
Tenalif® - Adults
Tesaperlas

Expectorante & Supresor de la Tos
Expectorant & Cough Suppressant

Controls cough
Controla la tos

Thins & loosens mucus
Adelgaza y expulsa las flemas

SOFTGELS
Dextromethorphan HBr 20 mg / Guaifenesin 400 mg
20 Softgels Box